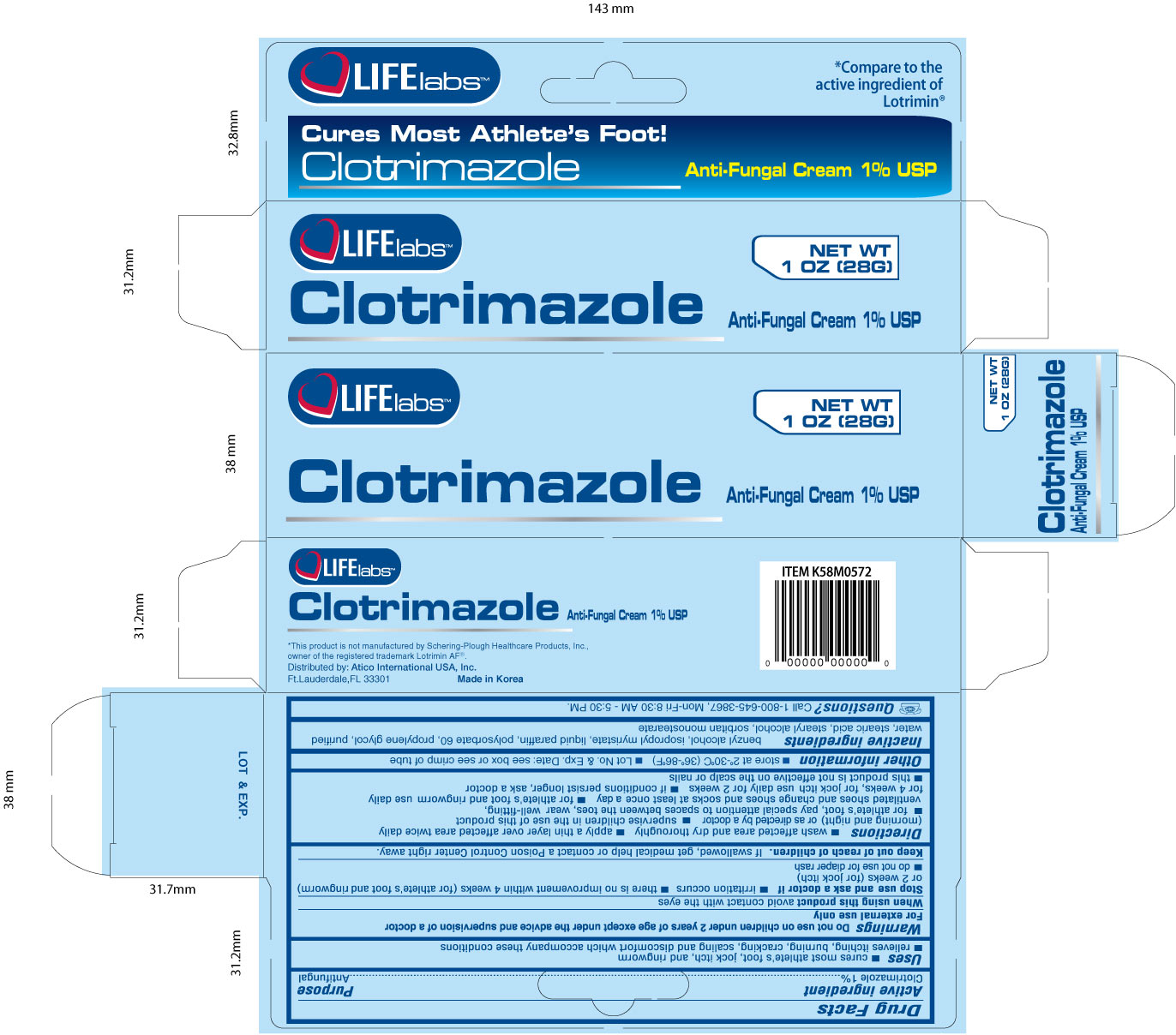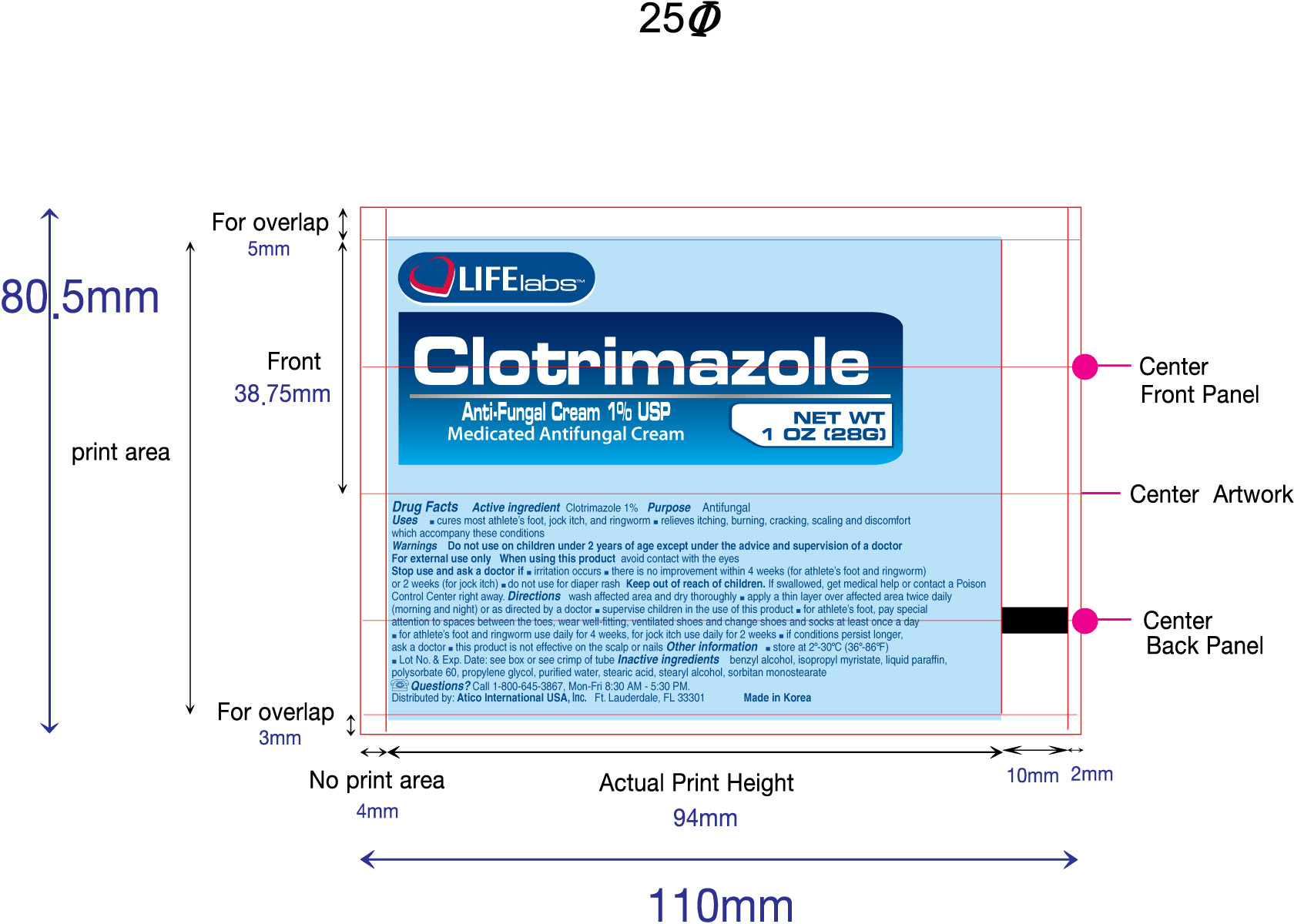 DRUG LABEL: Clotrimazole
NDC: 51852-103 | Form: CREAM
Manufacturer: LIFElabs, a Division of Atico International USA, INC.
Category: otc | Type: HUMAN OTC DRUG LABEL
Date: 20100823

ACTIVE INGREDIENTS: Clotrimazole 10 mg/1 g
INACTIVE INGREDIENTS: Benzyl Alcohol; Isopropyl Myristate; Mineral Oil; Polysorbate 60; Propylene Glycol; Water; Stearic Acid; Stearyl Alcohol; Sorbitan Monostearate

LIFElabs, a Division of Atico International USA, INC.

Clotrimazole

Active Ingredient

Clotrimazole 1%

Purpose

Antifungal

Uses

- cures most athlete's foot, jock itch, and ringworm
- relieves itching, burning, cracking, scaling and discomfort which accompany these conditions

Warnings

Do not use on children under 2 years of age except under the advice and supervision of a doctor.

For external use only.

When using this product avoid contact with the eyes.

Stop use and ask a doctor if

- irritation occurs
- there is no improvement within 4 weeks (for athlete's foot and ringworm) or 2 weeks (for jock itch)
- do not use for diaper rash

Keep out of reach of children. If swallowed, get medical help or contact a Poison Control Center right away.

Directions

- wash affected area and dry thoroughly
- apply a thin layer over affected area twice daily (morning and night) or as directed by a doctor
- supervise children in the use of this product
- for athlete's foot, pay special attention to spaces between the toes, wear well-fitting, ventilated shoes and change shoes and socks at least once a day
- for athlete's foot and ringworm use daily for 4 weeks, for jock itch use daily for 2 weeks
- if conditions persist longer, ask a doctor
- this product is not effective on the scalp or nails

Other information

store between 2o and 30o C (30o and 86o F) Lot No. and Exp. Date: see box or see crimp of tube

Inactive ingredients

benzyl alcohol, isopropyl myristate, liquid parafin, polysorbate 60, propylene glycol, purified water, stearic acid, stearyl aclohol, sorbitan monostearate

Questions?

Call 1-800-645-3867, Mon-Fri 8:30 AM - 5:30 PM.